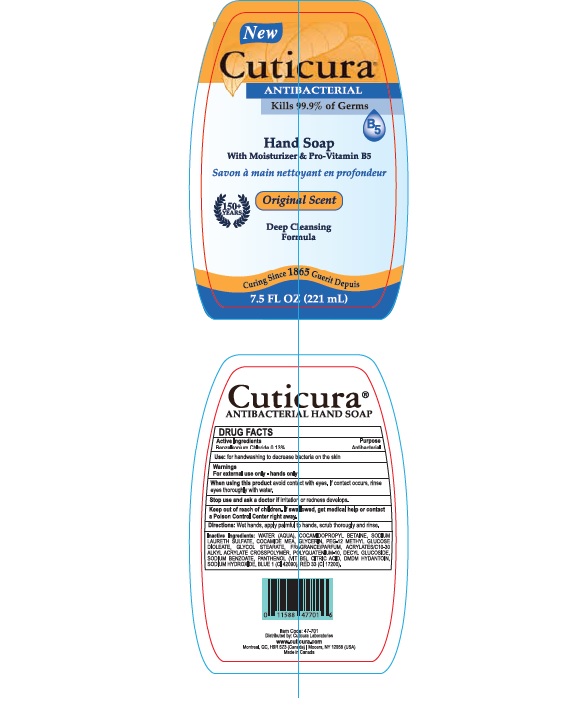 DRUG LABEL: Benzalkonium Chloride
NDC: 50157-210 | Form: LIQUID
Manufacturer: Brands International Corporation
Category: otc | Type: HUMAN OTC DRUG LABEL
Date: 20180501

ACTIVE INGREDIENTS: BENZALKONIUM CHLORIDE 1.3 mg/1 mL
INACTIVE INGREDIENTS: WATER; CITRIC ACID ACETATE; DECYL GLUCOSIDE; DMDM HYDANTOIN; POLYQUATERNIUM-10 (1000 MPA.S AT 2%); SODIUM LAURETH SULFATE; SODIUM CHLORIDE; SODIUM BENZOATE; SODIUM HYDROXIDE; GLYCOL STEARATE; GLYCERIN; DITETRACYCLINE TETRASODIUM EDETATE; PANTHENOL; POLYETHYLENE GLYCOL 600; FD&C BLUE NO. 1; FD&C RED NO. 4; COCAMIDOPROPYL BETAINE; COCO MONOETHANOLAMIDE

Cuticura- Antibacterial Hand Soap with Moisturizer & Pro-Vitamin B5

ACTIVE INGREDIENT

Benzalkonium Chloride - 0.13%

Purpose - Antibacterial

INDICATIONS AND USAGE

Use for handwashing to decrease bacteria on the skin

WARNINGS

Warning - For external use only - hands only

When using this product avoid contact with eyes. If contact occurs, rinse eyes thoroughly with water

Stop use and ask a doctor if

- irritaion or redness develops
- condition persists for more than 72 hours

Keep out of reach of children. If swallowed, get medical help or contact a Poison Control Center right away

Directions

- Wet Hands
- Apply palmful to hands
- scrub thoroughly
- rinse thoroughly

INACTIVE INGREDIENT

Inactive Ingredients: Water (Aqua),Acrylates/C10-30 Alkyl Acrylate crosspolymer, Citrtic Acid, Cocamidopropyl Betaine,Cocamide MEA,Decyl Glucoside, DMDM Hydantoin,Sodium Benzoate, Sodium Laureth Sulfate, Sodium Chloride, Sodium Hydroxide, Glycerin, Fragrance,Panthenol (Parfum),PEG-12 Methyl Glucose Dioleate, Polyquatenium 10, Tetrasodium EDTA, Blue 1, Red# 4 (Cl 14700)